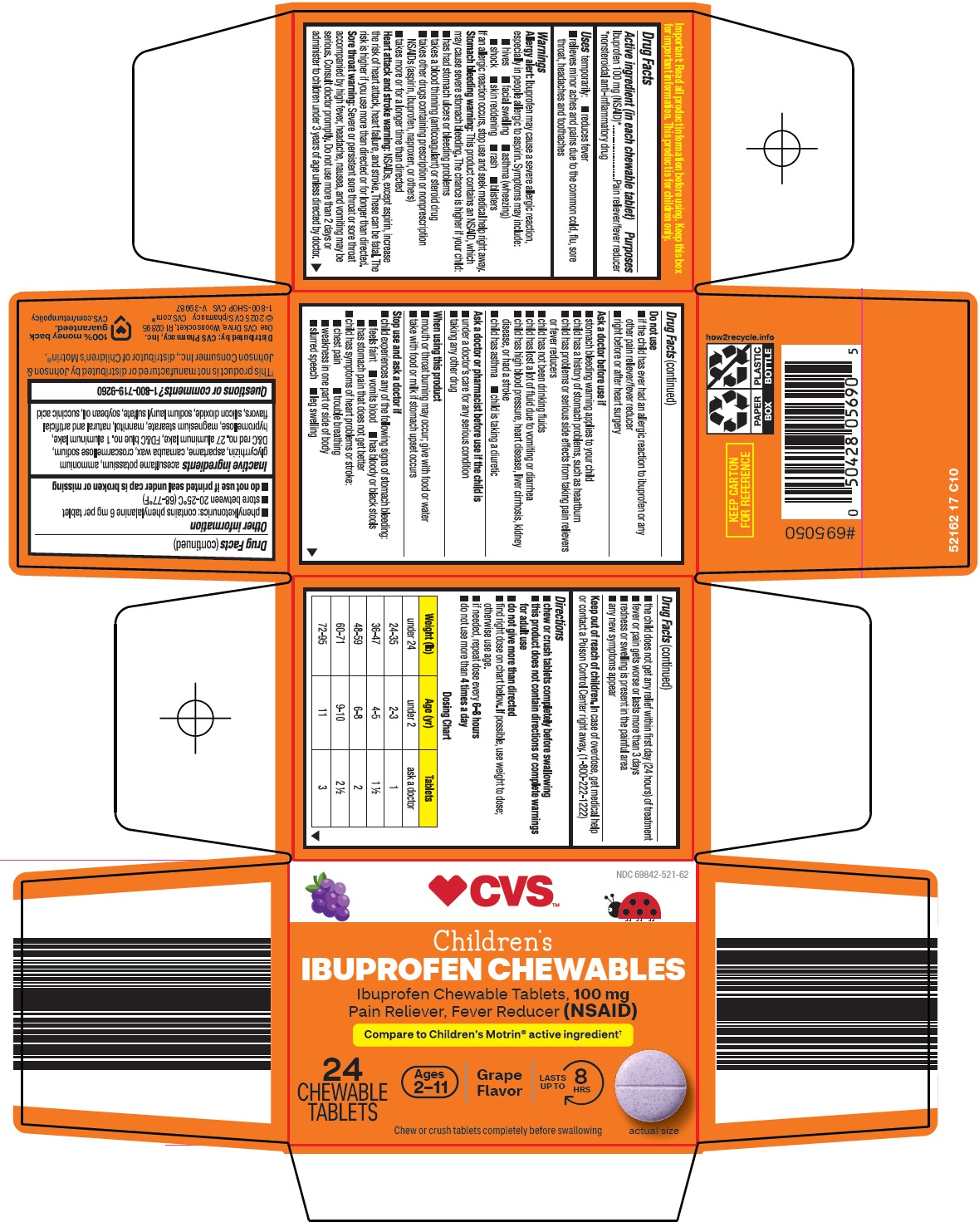 DRUG LABEL: childrens ibuprofen
NDC: 69842-521 | Form: TABLET, CHEWABLE
Manufacturer: CVS Pharmacy
Category: otc | Type: HUMAN OTC DRUG LABEL
Date: 20260227

ACTIVE INGREDIENTS: IBUPROFEN 100 mg/1 1
INACTIVE INGREDIENTS: ACESULFAME POTASSIUM; AMMONIUM GLYCYRRHIZATE; ASPARTAME; CARNAUBA WAX; CROSCARMELLOSE SODIUM; D&C RED NO. 27 ALUMINUM LAKE; FD&C BLUE NO. 1 ALUMINUM LAKE; HYPROMELLOSE, UNSPECIFIED; MAGNESIUM STEARATE; MANNITOL; SILICON DIOXIDE; SODIUM LAURYL SULFATE; SOYBEAN OIL; SUCCINIC ACID

CVS Pharmacy, Inc. Children’s Ibuprofen Chewables Drug Facts

Active ingredient (in each chewable tablet)

Ibuprofen 100 mg (NSAID)*

*nonsteroidal anti-inflammatory drug

Purposes

Pain reliever/fever reducer

Uses

temporarily:

- reduces fever
- relieves minor aches and pains due to the common cold, flu, sore throat, headaches and toothaches

Warnings

Allergy alert: Ibuprofen may cause a severe allergic reaction, especially in people allergic to aspirin. Symptoms may include:

- hives
- facial swelling
- asthma (wheezing)
- shock
- skin reddening
- rash
- blisters

If an allergic reaction occurs, stop use and seek medical help right away.

Stomach bleeding warning: This product contains an NSAID, which may cause severe stomach bleeding. The chance is higher if your child:

- has had stomach ulcers or bleeding problems
- takes a blood thinning (anticoagulant) or steroid drug
- takes other drugs containing prescription or nonprescription NSAIDs (aspirin, ibuprofen, naproxen, or others)
- takes more or for a longer time than directed

Heart attack and stroke warning: NSAIDs, except aspirin, increase the risk of heart attack, heart failure, and stroke. These can be fatal. The risk is higher if you use more than directed or for longer than directed.

Sore throat warning: Severe or persistent sore throat or sore throat accompanied by high fever, headache, nausea, and vomiting may be serious. Consult doctor promptly. Do not use more than 2 days or administer to children under 3 years of age unless directed by a doctor.

Do not use

- if the child has ever had an allergic reaction to ibuprofen or any other pain reliever/fever reducer
- right before or after heart surgery

Ask a doctor before use if

- stomach bleeding warning applies to your child
- child has a history of stomach problems, such as heartburn
- child has problems or serious side effects from taking pain relievers or fever reducers
- child has not been drinking fluids
- child has lost a lot of fluid due to vomiting or diarrhea
- child has high blood pressure, heart disease, liver cirrhosis, kidney disease, or had a stroke
- child has asthma
- child is taking a diuretic

Ask a doctor or pharmacist before use if the child is

- under a doctor’s care for any serious condition
- taking any other drug

When using this product

- mouth or throat burning may occur; give with food or water
- take with food or milk if stomach upset occurs

Stop use and ask a doctor if

- child experiences any of the following signs of stomach bleeding:
  - feels faint
  - vomits blood
  - has bloody or black stools
  - has stomach pain that does not get better
- child has symptoms of heart problems or stroke:
  - chest pain
  - trouble breathing
  - weakness in one part or side of body
  - slurred speech
  - leg swelling
- the child does not get any relief within first day (24 hours) of treatment
- fever or pain gets worse or lasts more than 3 days
- redness or swelling is present in the painful area
- any new symptoms appear

Keep out of reach of children.

In case of overdose, get medical help or contact a Poison Control Center right away. (1-800-222-1222)

Directions

- chew or crush tablets completely before swallowing
- this product does not contain directions or complete warnings for adult use
- do not give more than directed
- find right dose on chart below. If possible, use weight to dose; otherwise use age.
- if needed, repeat dose every 6-8 hours
- do not use more than 4 times a day

Dosing Chart
Weight (lb) | Age (yr) | Tablets
under 24 | under 2 | ask a doctor
24-35 | 2-3 | 1
36-47 | 4-5 | 1 ½
48-59 | 6-8 | 2
60-71 | 9-10 | 2 ½
72-95 | 11 | 3

Other information

- phenylketonurics: contains phenylalanine 6 mg per tablet
- store between 20-25°C (68-77°F)
- do not use if printed seal under cap is broken or missing

Inactive ingredients

acesulfame potassium, ammonium glycyrrhizin, aspartame, carnauba wax, croscarmellose sodium, D&C red no. 27 aluminum lake, FD&C blue no. 1 aluminum lake, hypromellose, magnesium stearate, mannitol, natural and artificial flavors, silicon dioxide, sodium lauryl sulfate, soybean oil, succinic acid

Questions or comments?

1-800-719-9260

Package/Label Principal Display Panel

CVS™

Children’s

IBUPROFEN CHEWABLES

Ibuprofen Chewable Tablets, 100 mg

Pain Reliever, Fever Reducer (NSAID)

Compare to Children’s Motrin® active ingredient

24 CHEWABLE TABLETS

Ages 2-11 | Grape Flavor | LASTS UP TO 8 HRS

Chew or crush tablets completely before swallowing

actual size